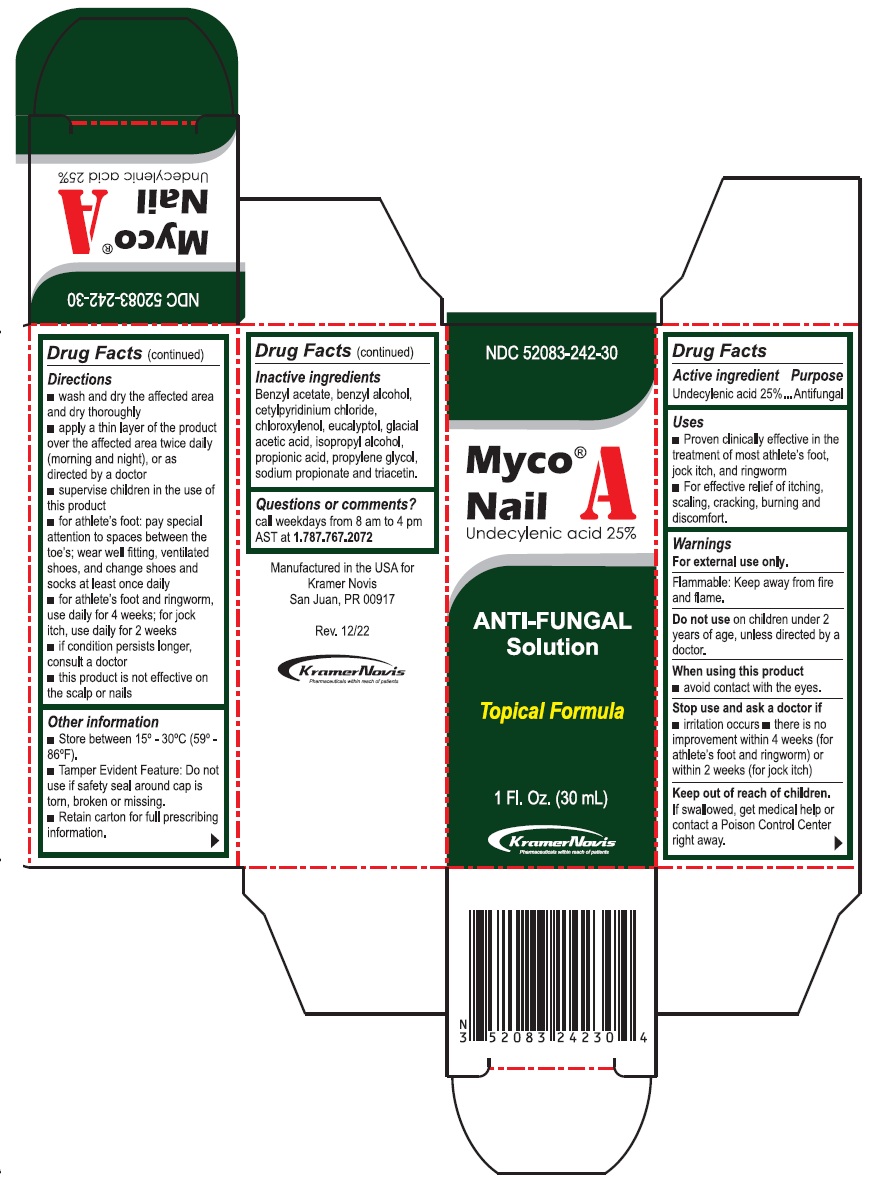 DRUG LABEL: Myco Nail A Antifungal Solution
NDC: 52083-242 | Form: LIQUID
Manufacturer: Kramer Novis
Category: otc | Type: HUMAN OTC DRUG LABEL
Date: 20251204

ACTIVE INGREDIENTS: UNDECYLENIC ACID 250 mg/1 mL
INACTIVE INGREDIENTS: BENZYL ACETATE; BENZYL ALCOHOL; CETYLPYRIDINIUM CHLORIDE; CHLOROXYLENOL; EUCALYPTOL; ACETIC ACID; ISOPROPYL ALCOHOL; PROPIONIC ACID; PROPYLENE GLYCOL; SODIUM PROPIONATE; TRIACETIN

Myco® Nail A
ANTI-FUNGAL Solution

Active ingredient

Undecylenic acid 25%

Purpose

Antifungal

Uses

• Proven clinically effective in the treatment of most athlete’s foot, jock itch, and ringworm
• For effective relief of itching, scaling, cracking, burning and discomfort.

Warnings

For external use only.

Flammable: Keep away from fire and flame.

Do not use on children under 2 years of age, unless directed by a doctor.

When using this product
• avoid contact with the eyes.

Stop use and ask a doctor if
• irritation occurs • there is no improvement within 4 weeks (for athlete’s foot and ringworm) or within 2 weeks (for jock itch)

Keep out of reach of children. If swallowed, get medical help or contact a Poison Control Center right away.

Directions

• wash and dry the affected area and dry thoroughly
• apply a thin layer of the product over the affected area twice daily (morning and night), or as directed by a doctor
• supervise children in the use of this product
• for athlete’s foot: pay special attention to spaces between the toes; wear well fitting, ventilated shoes, and change shoes and socks at least once daily
• for athlete’s foot and ringworm, use daily for 4 weeks; for jock itch, use daily for 2 weeks
• if condition persists longer, consult a doctor
• this product is not effective on the scalp or nails

Other information

• Store between 15° – 30°C (59° – 86°F).
• Tamper Evident Feature: Do not use if safety seal around cap is torn, broken or missing.
• Retain carton for full prescribing information.

Inactive ingredients

Benzyl acetate, benzyl alcohol, cetylpyridinium chloride, chloroxylenol, eucalyptol, glacial acetic acid, Isopropyl alcohol, propionic acid, propylene glycol, sodium propionate and triacetin.

Questions or comments?

call weekdays from 8 am to 4 pm AST at 1.787.767.2072

Manufactured in the USA for Kramer Novis
San Juan, PR 00917

KramerNovis
Pharmaceuticals within reach of patients